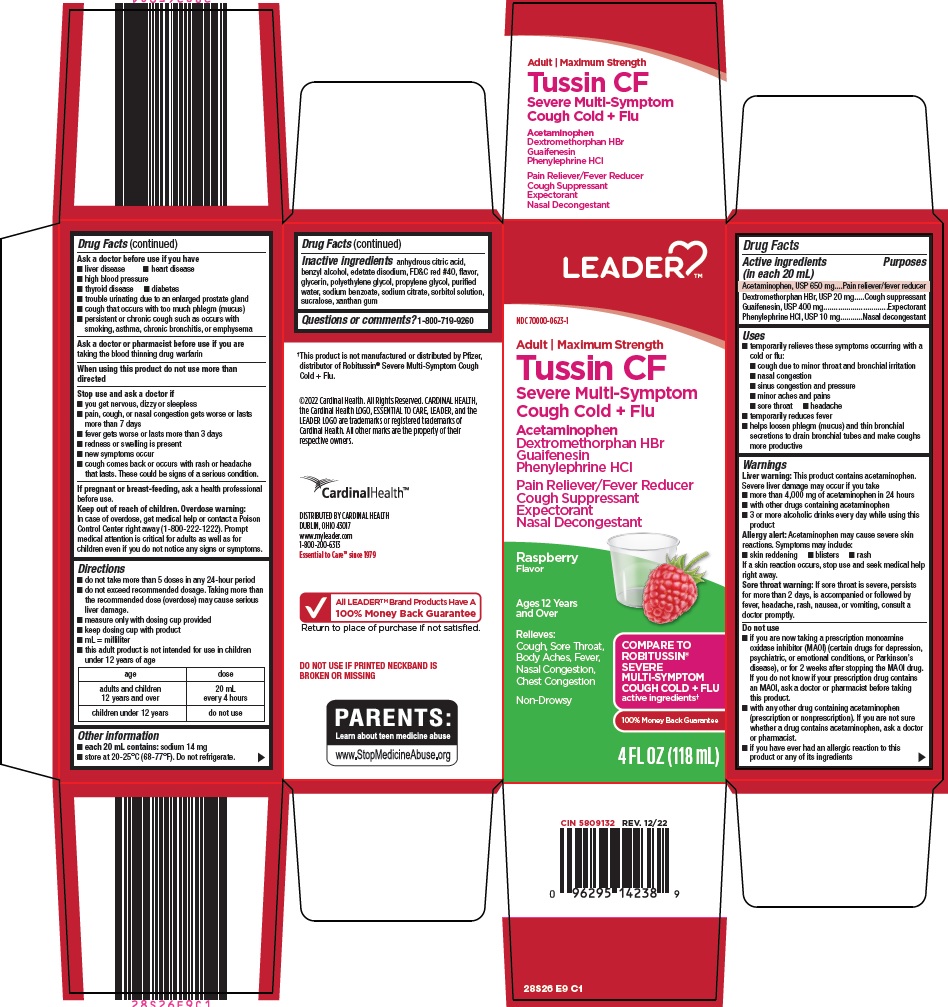 DRUG LABEL: leader tussin cf
NDC: 70000-0623 | Form: SOLUTION
Manufacturer: Cardinal Health 110, LLC. dba Leader
Category: otc | Type: HUMAN OTC DRUG LABEL
Date: 20260225

ACTIVE INGREDIENTS: ACETAMINOPHEN 650 mg/20 mL; DEXTROMETHORPHAN HYDROBROMIDE 20 mg/20 mL; GUAIFENESIN 400 mg/20 mL; PHENYLEPHRINE HYDROCHLORIDE 10 mg/20 mL
INACTIVE INGREDIENTS: ANHYDROUS CITRIC ACID; BENZYL ALCOHOL; EDETATE DISODIUM; FD&C RED NO. 40; GLYCERIN; POLYETHYLENE GLYCOL, UNSPECIFIED; PROPYLENE GLYCOL; WATER; SODIUM BENZOATE; SODIUM CITRATE, UNSPECIFIED FORM; SORBITOL; SUCRALOSE; XANTHAN GUM

Cardinal Health Tussin CF Drug Facts

Active ingredients (in each 20 mL)

Acetaminophen, USP 650 mg

Dextromethorphan HBr, USP 20 mg

Guaifenesin, USP 400 mg

Phenylephrine HCl, USP 10 mg

Purposes

Pain reliever/fever reducer

Cough suppressant

Expectorant

Nasal decongestant

Uses

- temporarily relieves these symptoms occurring with a cold or flu:
- cough due to minor throat and bronchial irritation
- nasal congestion
- sinus congestion and pressure
- minor aches and pains
- sore throat
- headache
- temporarily reduces fever
- helps loosen phlegm (mucus) and thin bronchial secretions to drain bronchial tubes and make coughs more productive

Warnings

Liver warning: This product contains acetaminophen. Severe liver damage may occur if you take

- more than 4,000 mg of acetaminophen in 24 hours
- with other drugs containing acetaminophen
- 3 or more alcoholic drinks every day while using this product

Allergy alert: Acetaminophen may cause severe skin reactions. Symptoms may include:

- skin reddening
- blisters
- rash

If a skin reaction occurs, stop use and seek medical help right away.

Sore throat warning: If sore throat is severe, persists for more than 2 days, is accompanied or followed by fever, headache, rash, nausea, or vomiting, consult a doctor promptly.

Do not use

- if you are now taking a prescription monoamine oxidase inhibitor (MAOI) (certain drugs for depression, psychiatric, or emotional conditions, or Parkinson’s disease), or for 2 weeks after stopping the MAOI drug. If you do not know if your prescription drug contains an MAOI, ask a doctor or pharmacist before taking this product.
- with any other drug containing acetaminophen (prescription or nonprescription). If you are not sure whether a drug contains acetaminophen, ask a doctor or pharmacist.
- if you have ever had an allergic reaction to this product or any of its ingredients

Ask a doctor before use if you have

- liver disease
- heart disease
- high blood pressure
- thyroid disease
- diabetes
- trouble urinating due to an enlarged prostate gland
- cough that occurs with too much phlegm (mucus)
- persistent or chronic cough such as occurs with smoking, asthma, chronic bronchitis, or emphysema

Ask a doctor or pharmacist before use if you are

taking the blood thinning drug warfarin

Stop use and ask a doctor if

- you get nervous, dizzy or sleepless
- pain, cough, or nasal congestion gets worse or lasts more than 7 days
- fever gets worse or lasts more than 3 days
- redness or swelling is present
- new symptoms occur
- cough comes back or occurs with rash or headache that lasts. These could be signs of a serious condition.

If pregnant or breast-feeding,

ask a health professional before use.

Keep out of reach of children.

Overdose warning: In case of overdose, get medical help or contact a Poison Control Center right away (1-800-222-1222). Prompt medical attention is critical for adults as well as for children even if you do not notice any signs or symptoms.

Directions

- do not take more than 5 doses in any 24-hour period
- do not exceed recommended dosage. Taking more than the recommended dose (overdose) may cause serious liver damage.
- measure only with dosing cup provided
- keep dosing cup with product
- mL = milliliter
- this adult product is not intended for use in children under 12 years of age

age | dose
adults and children; 12 years and over | 20 mL every 4 hours
children under 12 years | do not use

Other information

- each 20 mL contains: sodium 14 mg
- store at 20-25°C (68-77°F). Do not refrigerate.

Inactive ingredients

anhydrous citric acid, benzyl alcohol, edetate disodium, FD&C red #40, flavor, glycerin, polyethylene glycol, propylene glycol, purified water, sodium benzoate, sodium citrate, sorbitol solution, sucralose, xanthan gum

Questions or comments?

1-800-719-9260

Package/Label Principal Display Panel

Leader™

Adult | Maximum Strength

Tussin CF

Severe Multi-Symptom Cough Cold + Flu

Acetaminophen

Dextromethorphan HBr

Guaifenesin

Phenylephrine HCl

Pain Reliever/Fever Reducer

Cough Suppressant

Expectorant

Nasal Decongestant

Raspberry Flavor

Ages 12 Years and Over

Relieves:

Cough, Sore Throat, Body Aches, Fever, Nasal Congestion, Chest Congestion

Non-Drowsy

COMPARE TO ROBITUSSIN® SEVERE MULTI-SYMPTOM COUGH COLD + FLU

active ingredients

100% Money Back Guarantee

4 FL OZ (118 mL)